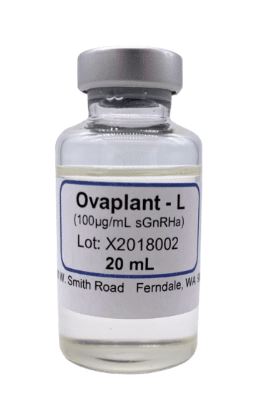 DRUG LABEL: Ovaplant-L
NDC: 50378-017 | Form: LIQUID, EXTENDED RELEASE
Manufacturer: Western Chemical Inc.
Category: animal | Type: OTC ANIMAL DRUG LABEL
Date: 20230621

ACTIVE INGREDIENTS: SALMON GONADOTROPIN RELEASING HORMONE D-ARG6 ANALOG ETHYL AMIDE ACETATE 0.002 g/1 mL
INACTIVE INGREDIENTS: SUCROSE ACETATE ISOBUTYRATE 14 g/1 mL; PROPYLENE CARBONATE 6 g/1 mL

Ovaplant-L

Ovaplant-L.jpg

Add image transcription here...